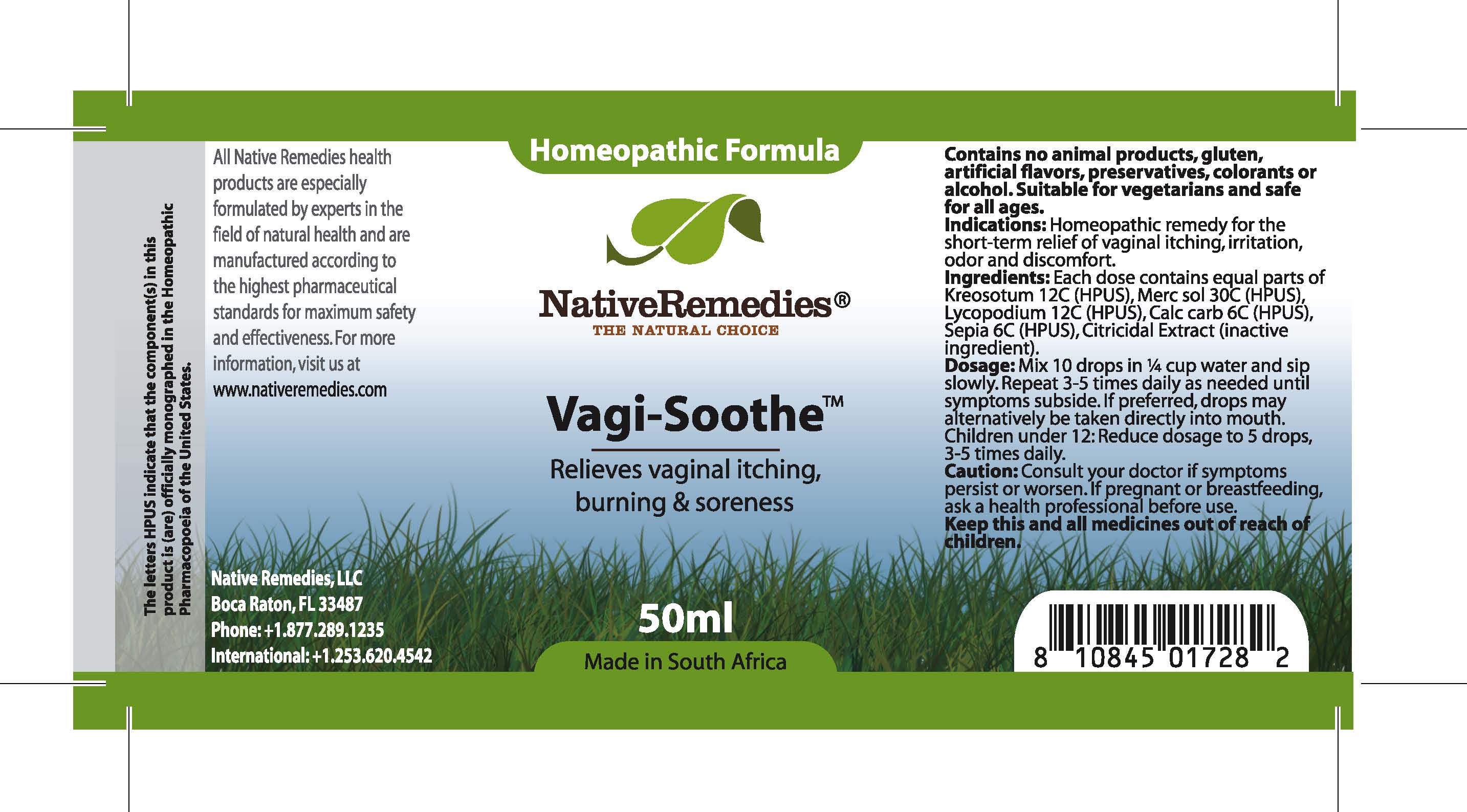 DRUG LABEL: Vagi Soothe
NDC: 68647-176 | Form: TINCTURE
Manufacturer: Feelgood Health
Category: homeopathic | Type: HUMAN OTC DRUG LABEL
Date: 20100902

ACTIVE INGREDIENTS: LARREA TRIDENTATA TOP 12 [hp_C]/40 mL; MERCURIUS SOLUBILIS 30 [hp_C]/40 mL; LYCOPODIUM CLAVATUM SPORE 12 [hp_C]/40 mL; CALCIUM CARBONATE 6 [hp_C]/40 mL; ACANTHOSEPION CUTTLEFISH 6 [hp_C]/40 mL
INACTIVE INGREDIENTS: CITRUS PARADISI SEED 0.125 mL/50 mL; WATER 49.486 mL/50 mL

VAGISOOTHE

PURPOSE

Relieves vaginal itching, burning and soreness

INDICATIONS AND USAGE

Indications: Homeopathic remedy for the relief of vaginal itching, irritation, odor and discomfort.

DOSAGE AND ADMINISTRATION

Dosage: Mix 10 drops in ¼ cup water and sip slowly. Repeat 3-5 times daily as needed until symptoms subside. If preferred, drops may be taken directly into the mouth. Children under 12: Reduce dosage to 5 drops, 3-5 times daily.

GENERAL PRECAUTIONS

Caution: Consult your doctor if symptoms persist or worsen. If pregnant or breastfeeding, ask a health professional before use. Keep this and all medicines out of reach of children.

ACTIVE INGREDIENT

Ingredients: Each dose contains equal parts of Kreosotum (12C) (HPUS), Merc sol (30C) (HPUS), Lycopodium (12C) (HPUS), Calc carb (6C) (HPUS), Sepia (6C) (HPUS)

Citricidal extract (inactive ingredient).

PREGNANCY

If pregnant or breastfeeding, ask a health professional before use.

WARNINGS

Contains no animal products, gluten, artificial flavors, preservatives, colorants or alcohol. Suitable for vegetarians and safe for all ages.

PATIENT COUNSELING INFORMATION

All Native Remedies health products are especially formulated by experts in the field of natural health and are manufactured according to the highest pharmaceutical standards for maximum safety and effectiveness. For more information, visit us at www.nativeremedies.com

Distributed by

Native Remedies, LLC

6531 Park of Commerce Blvd.

Suite 160

Boca Raton, FL 33487

Phone: 1.877.289.1235

International: + 1.561.999.8857

The letters HPUS indicate that the component(s) in this product is (are) officially monographed in the Homeopathic Pharmacopoeia of the United States.

KEEP OUT OF REACH OF CHILDREN

Keep this and all medicines out of reach of children.